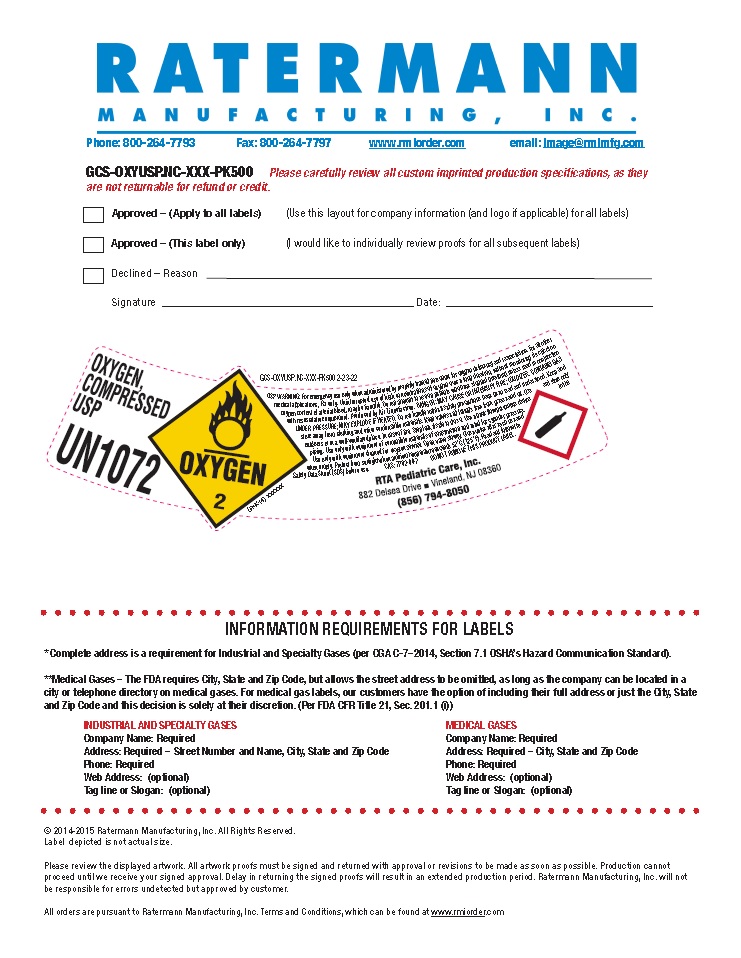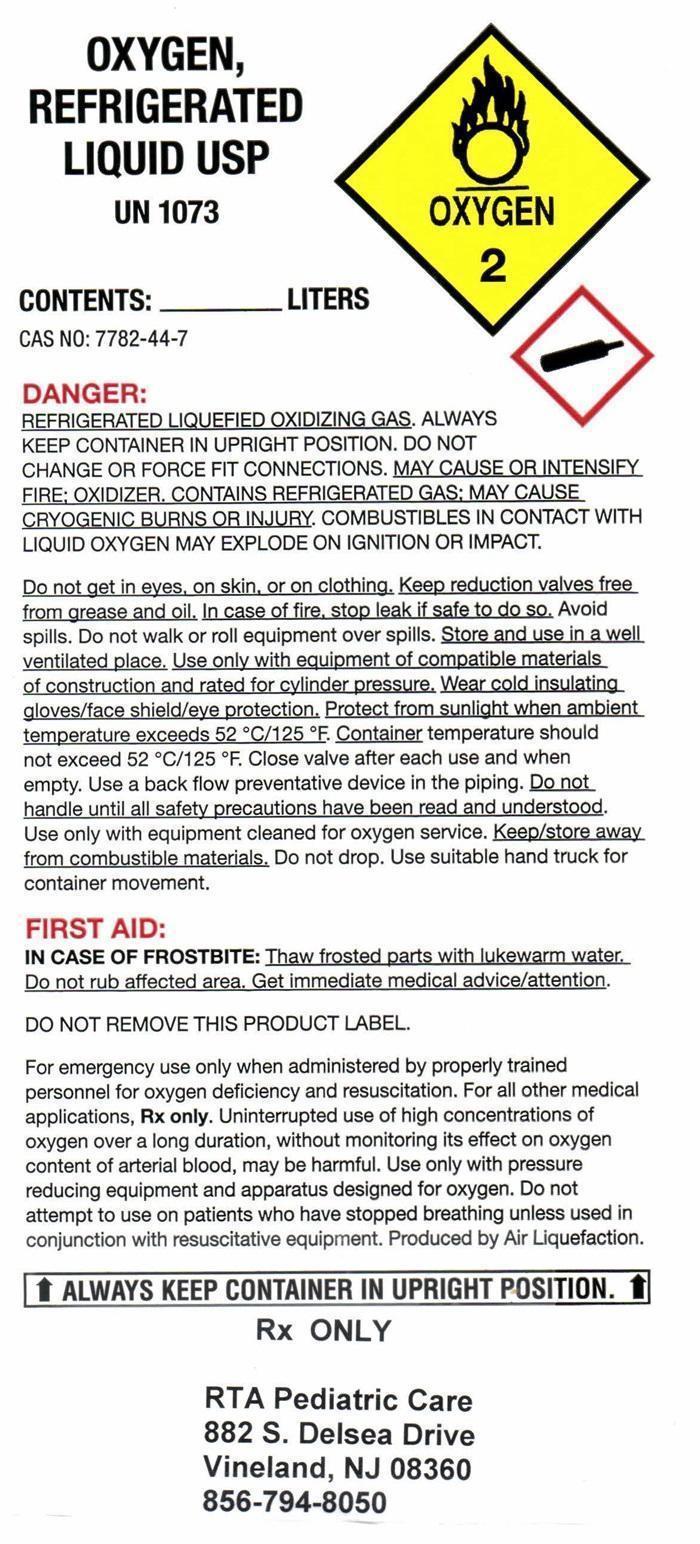 DRUG LABEL: OXYGEN
NDC: 69241-001 | Form: GAS
Manufacturer: RTA Pediatric Care Inc.
Category: prescription | Type: HUMAN PRESCRIPTION DRUG LABEL
Date: 20251111

ACTIVE INGREDIENTS: OXYGEN 99 L/100 L

OXYGEN USP Label

OXYGEN REFRIGERATED LIQUID USP
UN 1073
CONTENTS: _________ LITERS
CAS NO: 7782-44-7
DANGER:
REFRIGERATED LIQUEFIED OXIDIZING GAS. ALWAYS KEEP CONTAINER IN UPRIGHT POSITION. DO NOT CHANGE OR FORCE FIT CONNECTIONS. MAY CAUSE OR INTENSIFY FIRE: OXIDIZER, CONTAINS REFRIGERATED GAS: MAY CAUSE CRYOGENIC BURNS OR INJURY. COMBUSTIBLES IN CONTACT WITH LIQUID OXYGEN MAY EXPLODE ON IGNITION OR IMPACT.
Do not get in eyes, on skin, or on clothing. Keep reduction valves free from grease and oil. In case of fire, stop leak if it is safe to do so. Avoid spills.Do not walk or roll equipment over spills. Store and use in a well ventilated place. Use only with equipment of compatible materials of construction and rated for cylinder pressure. Wear cold insulating gloves/face shield/eye protection. Protect from sunlight when ambient temperature exceeds 52° C/125° F. Container temperature should not exceed 52° C/125° F. Close valve after each use and when empty. Use a back flow preventive device in the piping. Do not handle until all safety precautions have been read and understood. Use only with equipment cleaned or oxygen service. Keep/store away from combustible materials. Do not drop. Use suitable hand truck for container movement.
FIRST AID:
IN CASE OF FROSTBITE: Thaw frosted parts with lukewarm water. Do not rub affected area. Get immediate medical advice/attention.
DO NOT REMOVE THIS PRODUCT LABEL.
For emergency use only when administered by properly trained personnel for oxygen deficiency and resuscitation. For all other medical applications, Rx only. Uninterrupted use of high concentrations of oxygen over a long duration, without monitoring its effect on oxygen content of arterial blood, may be harmful. use only with pressure reducing equipment and apparatus designed for oxygen. Do not attempt to use on patients who have stopped breathing unless used in conjunction with resuscitative equipment. Produced by Air Liquefaction.
↑ALWAYS KEEP CONTAINER IN UPRIGHT POSITION.↑
Rx ONLY
RTA Pediatric Care
882 S. Delsea Drive
Vineland, NJ 08360
856-794-8050

OXYGEN, COMPRESSED USP LABEL

OXYGEN, COMPRESSED USP

UN1072

RTA Pediatric Care
882 S. Delsea Drive
Vineland, NJ 08360
856-794-8050

res